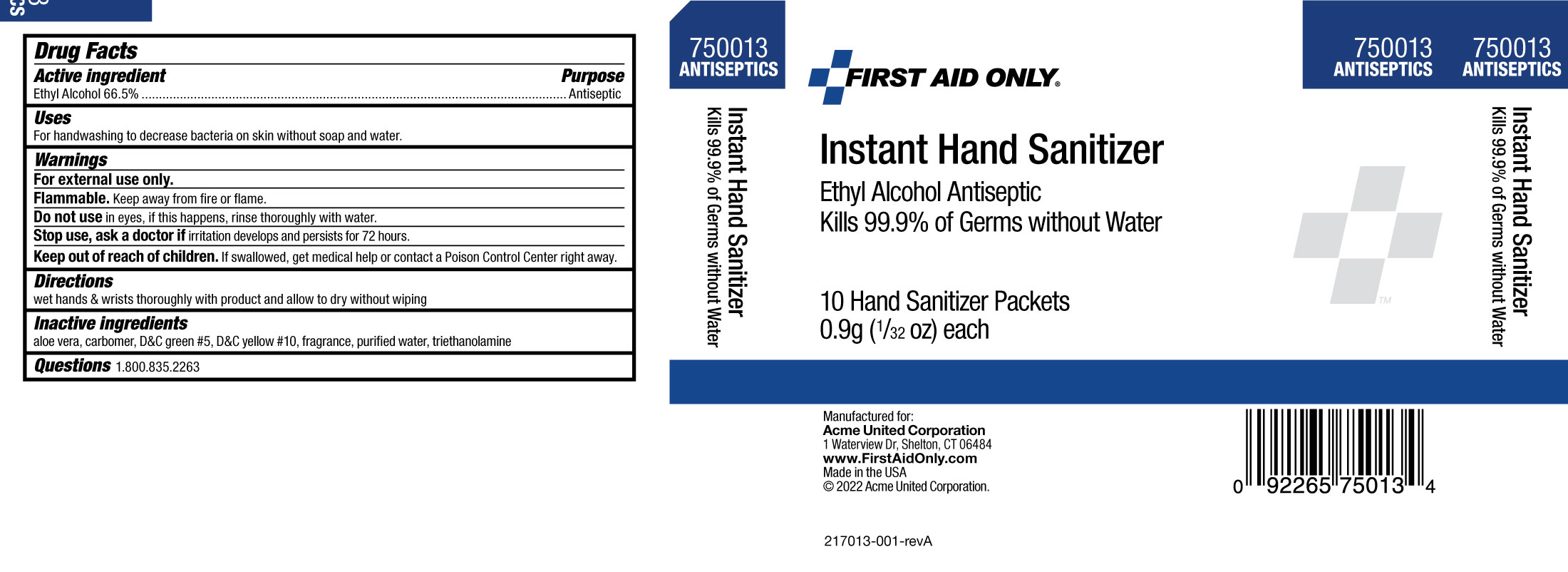 DRUG LABEL: First Aid Only Instant Hand Sanitizer
NDC: 0924-0450 | Form: GEL
Manufacturer: Acme United Corporation
Category: otc | Type: HUMAN OTC DRUG LABEL
Date: 20241126

ACTIVE INGREDIENTS: ALCOHOL 665 mL/1 L
INACTIVE INGREDIENTS: D&C GREEN NO. 5; D&C YELLOW NO. 10; ALOE; WATER; TROLAMINE; FRAGRANCE 13576; CARBOMER 980

First Aid Only Instant Hand Sanitizer

Drug Facts

Active ingredient

Ethyl Alcohol 66.5%

Purpose

Antiseptic

Uses

For handwashing to decrease bacteria on skin without soap and water.

.

Warnings

For External use only.

Flammable. keep away from fire or flame.

Do not use in eyes. If this happens, rinse thoroughly with water.

Stop use, ask a doctor if irritation develops and persists for more than 72 hours.

Keep out of reach of children.

If swallowed, get medical help or contact a Poison Control Center right away.

Directions

- wet hands & wrists thoroughly with product and allow to dry without wiping

Inactive ingredients

aloe vera, carbomer, D&C green #5, D&C yellow #10, fragrance, purified water, triethanolamine

Questions 1.800.835.2263

Box Label